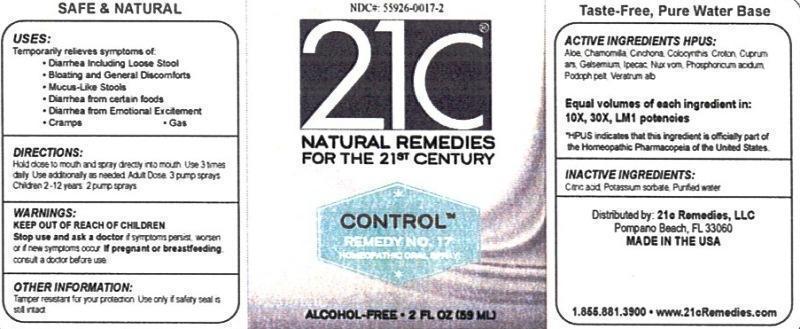 DRUG LABEL: Control Remedy No. 17
NDC: 55926-0017 | Form: LIQUID
Manufacturer: Speer Laboratories, LLC
Category: homeopathic | Type: HUMAN OTC DRUG LABEL
Date: 20130730

ACTIVE INGREDIENTS: ALOE 10 [hp_X]/59 mL; MATRICARIA RECUTITA 10 [hp_X]/59 mL; CINCHONA OFFICINALIS BARK 10 [hp_X]/59 mL; CITRULLUS COLOCYNTHIS FRUIT PULP 10 [hp_X]/59 mL; CROTON TIGLIUM SEED 10 [hp_X]/59 mL; CUPRIC ARSENITE 10 [hp_X]/59 mL; GELSEMIUM SEMPERVIRENS ROOT 10 [hp_X]/59 mL; IPECAC 10 [hp_X]/59 mL; STRYCHNOS NUX-VOMICA SEED 10 [hp_X]/59 mL; PHOSPHORIC ACID 10 [hp_X]/59 mL; PODOPHYLLUM 10 [hp_X]/59 mL; VERATRUM ALBUM ROOT 10 [hp_X]/59 mL
INACTIVE INGREDIENTS: CITRIC ACID MONOHYDRATE; POTASSIUM SORBATE; WATER

Control Remedy No. 17

ACTIVE INGREDIENT

Active Ingredients HPUS: Aloe socotrina, Chamomilla, Cinchona officinalis, Colocynthis, Crotontiglium, Cuprum arsenicosum, Gelsemium sempervirens, Ipecacuanha, Nux vomica, Phosphoricum acidum, Podophyllum peltatum Veratrum album.

Equal volumes of each ingredient in: 10X, 30X, LM1 potencies

HPUS indicates that this ingredient is officially part of the Homeopathic Pharmacopeia of the United States.

Inactive Ingredients: Citric acid, Potassium sorbate, Purified water.

INDICATIONS AND USAGE

Uses: Temporarily relieves symptoms of:

- Diarrhea including loose stool
- Bloating and general discomforts
- Mucus-like stools
- Diarrhea from certain foods
- Diarrhea from emotional excitement
- Cramps
- Gas

Directions:

Hold close to mouth and spray directly into mouth. Use 3 times daily. Use additionally as needed. Adult dose 3 pump sprays. Children 2-12 years 2 pump sprays

Keep out of reach of children.

WARNINGS

Warnings: Stop use and ask a doctor if symptoms persist, worsen or if new symptoms occur. If pregnant or breastfeeding, consult a doctor before use.

OTHER SAFETY INFORMATION

Tamper resistant for your protection. Use only if safety seal is still intact.

PURPOSE

Uses: Temporarily relieves symptoms of: Diarrhea including loose stool, bloating and general discomforts, mucus-like stools, diarrhea from certain foods, diarrhea from emotional excitement, cramps and gas.